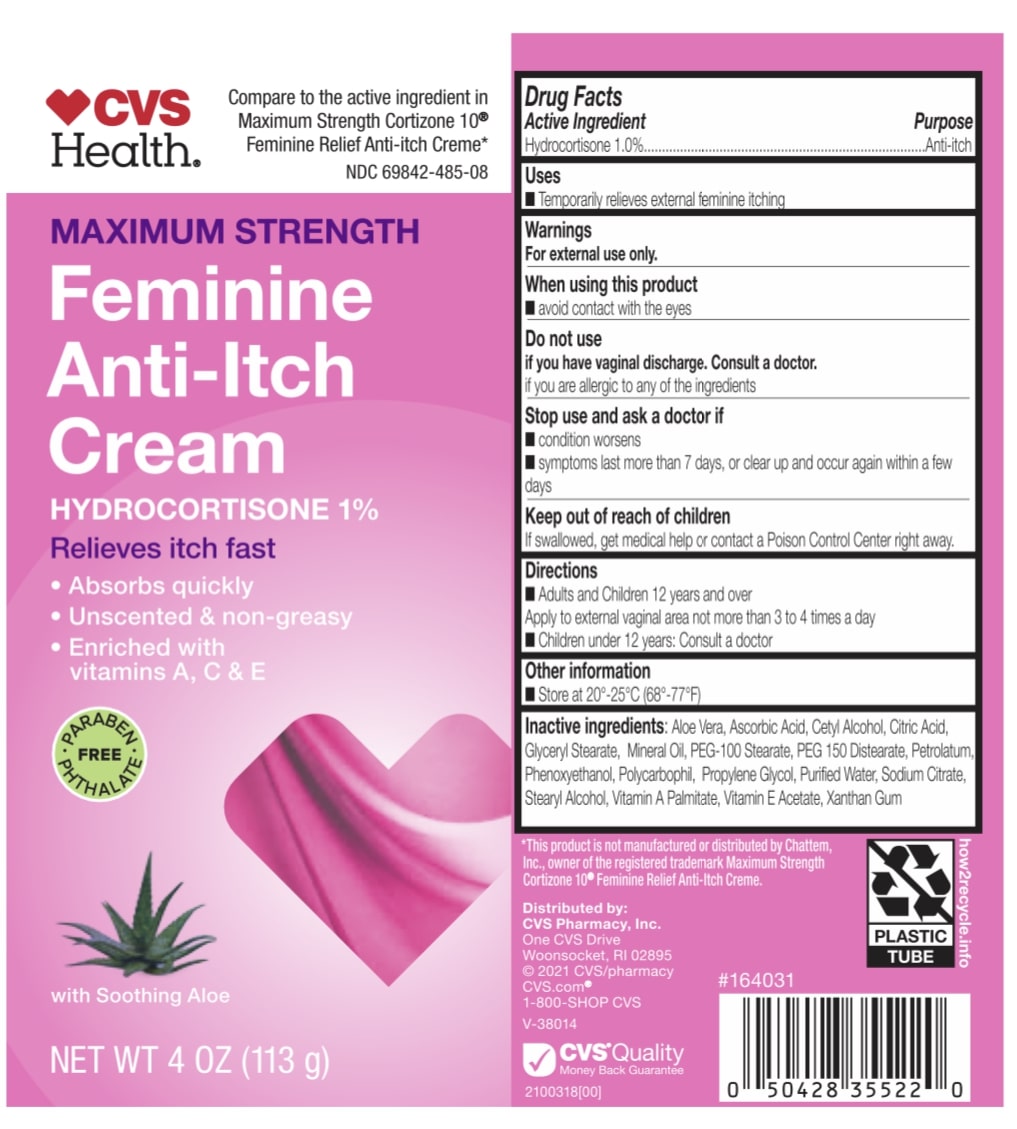 DRUG LABEL: CVS Maximum Strength Anti-Itch Cream
NDC: 69842-485 | Form: CREAM
Manufacturer: CVS Health
Category: otc | Type: HUMAN OTC DRUG LABEL
Date: 20241216

ACTIVE INGREDIENTS: HYDROCORTISONE 10 mg/1 g
INACTIVE INGREDIENTS: POLYCARBOPHIL; PROPYLENE GLYCOL; MINERAL OIL; CETYL ALCOHOL; WATER; CITRIC ACID MONOHYDRATE; PEG-150 DISTEARATE; ASCORBIC ACID; VITAMIN A PALMITATE; SODIUM CITRATE; XANTHAN GUM; STEARYL ALCOHOL; PETROLATUM; ALPHA-TOCOPHEROL ACETATE; ALOE VERA LEAF

ACTIVE INGREDIENT

Hydrocortisone 1.0%

PURPOSE

Anti-itch

INDICATIONS AND USAGE

Temporarily relieves external feminine itching

WARNINGS

WHEN USING

Avoid contact with the eyes

DO NOT USE

If you are allergic to any of the ingredients

Stop use and ask the doctor if :

- conditions worsen
- symptoms last ore than 7 days, or clear up and occur again within a few days

KEEP OUT OF REACH OF CHILDREN

If swallowed, get medical help or contact a poison control center right away.

DOSAGE AND ADMINISTRATION

- Adults and children 12 years and over: Apply to the external vaginal area more than 3 times a day
- Children under 12 years: Consult a doctor

OTHER SAFETY INFORMATION

Store at 20-25 C (68-77 F)

INACTIVE INGREDIENT

aloe vera, Ascorbic acid, Cetyl alcohol, Citric acid, Glyceryl stearate, Mineral oil, PEG-100 Stearate, PEG-150 Distearate, Petrolatum, Phenoxyethanol, Polycarbophil, Propylene Glycol, Purified Water, Sodium citrate, Stearyl alcohol, Vitamin A palmitate, Vitamin E acetate, Xanthan Gum.